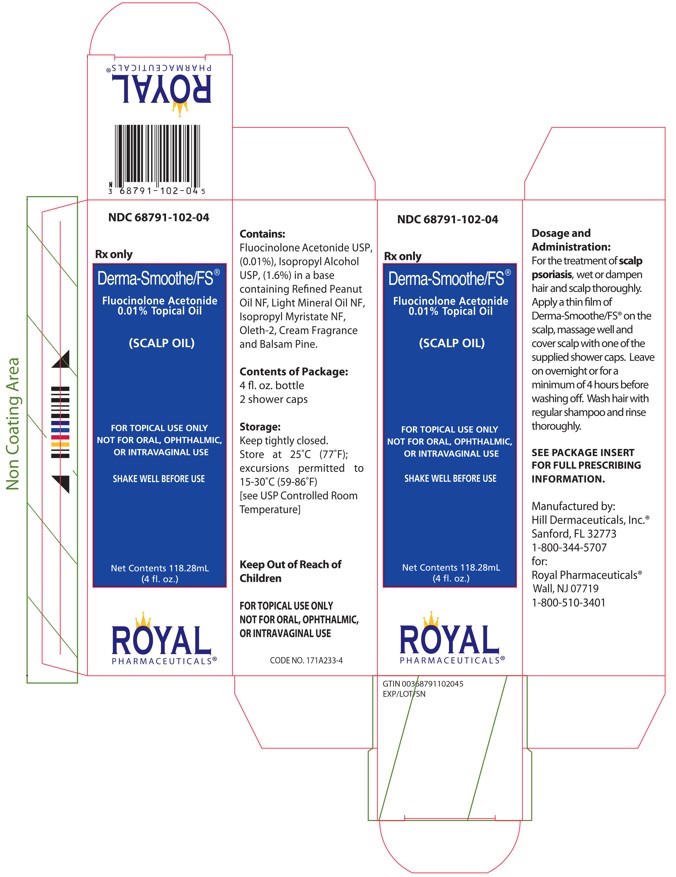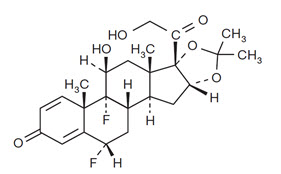 DRUG LABEL: DERMA-SMOOTHE/FS
NDC: 68791-102 | Form: OIL
Manufacturer: Royal Pharmaceuticals
Category: prescription | Type: HUMAN PRESCRIPTION DRUG LABEL
Date: 20250701

ACTIVE INGREDIENTS: fluocinolone acetonide 0.11 mg/1 mL
INACTIVE INGREDIENTS: ISOPROPYL ALCOHOL; ISOPROPYL MYRISTATE; LIGHT MINERAL OIL; OLETH-2; PEANUT OIL

HIGHLIGHTS OF PRESCRIBING INFORMATION

These highlights do not include all the information needed to use DERMA-SMOOTHE/FS Scalp Oil safely and effectively. See full prescribing information for DERMA-SMOOTHE/FS Scalp Oil.
DERMA-SMOOTHE/FS Scalp Oil (fluocinolone acetonide) topical oil
Initial U.S. Approval: 1988

1 INDICATIONS AND USAGE

Derma-Smoothe/FS® Scalp Oil is a corticosteroid indicated for the treatment of psoriasis of the scalp in adults. (1)

2 DOSAGE AND ADMINISTRATION

- DERMA-SMOOTHE/FS Scalp Oil is not for oral, ophthalmic, or intravaginal use. (2)
- Do not use on face or intertriginous areas. (2)
- Apply a thin film of DERMA-SMOOTHE/FS Scalp Oil on the wet scalp, massage well and cover scalp with the supplied shower cap. Leave on overnight or for a minimum of 4 hours before washing off. (2)

3 DOSAGE FORMS AND STRENGTHS

DERMA-SMOOTHE/FS Scalp Oil is a topical oil containing 0.01% fluocinolone acetonide, supplied in bottles containing 4 fluid ounces and with 2 shower caps. (3)

4 CONTRAINDICATIONS

None. (4)

5 WARNINGS AND PRECAUTIONS

- Endocrine System Adverse Reactions:
  o Topical corticosteroids can produce reversible HPA axis suppression, Cushing's syndrome, hyperglycemia, and glucosuria. (5.1)
  o Systemic absorption may require evaluation for hypothalamic-pituitary-adrenal (HPA) axis suppression. Potent corticosteroids use on large areas, prolonged use or occlusive use, altered skin barrier, liver failure, and young age may increase systemic absorption. Modify use should HPA axis suppression develop. (5.1)
- Local Adverse Reactions: Local adverse reactions may include atrophy, striae irritation, acneiform eruptions, hypopigmentation, and allergic contact dermatitis, and may be more likely with occlusive use or more potent corticosteroids. (5.2, 6.1)
- Ophthalmic Adverse Reactions: May increase the risks of glaucoma and posterior subcapsular cataract. Avoid contact of DERMA-SMOOTHE/FS Scalp Oil with eyes. Advise patients to report any visual symptoms and consider referral to an ophthalmologist for evaluation. (5.3)

6 ADVERSE REACTIONS

The most common adverse reactions in pediatric subjects treated for atopic dermatitis (≥5%) were cough (20%), rhinorrhea (13%), pyrexia (10%), telangiectasia (7%), nasopharyngitis (7%), and hypopigmentation (7%). (6.1, 6.2)

To report SUSPECTED ADVERSE REACTIONS, contact Hill Dermaceuticals, Inc. at 1-800-344-5707 or FDA at 1-800-FDA-1088 or www.fda.gov/medwatch.

FULL PRESCRIBING INFORMATION

1 INDICATIONS AND USAGE

DERMA-SMOOTHE/FS® Scalp Oil is indicated for the treatment of psoriasis of the scalp in adults.

2 DOSAGE AND ADMINISTRATION

DERMA-SMOOTHE/FS Scalp Oil is for topical use only. Not for oral, ophthalmic, or intravaginal use.

Wet or dampen hair and scalp thoroughly. Apply a thin film of DERMA-SMOOTHE/FS Scalp Oil on the scalp, massage well and cover scalp with the supplied shower cap. Leave on overnight or for a minimum of 4 hours then wash hair with regular shampoo and rinse thoroughly. Use daily as needed.

Discontinue DERMA-SMOOTHE/FS Scalp Oil when control of disease is achieved within 2 weeks, or contact the healthcare provider if no improvement is seen within 2 weeks.

Do not use DERMA-SMOOTHE/FS Scalp Oil on the face unless directed by the healthcare provider. Do not apply to intertriginous areas due to the increased risk of local adverse reactions [see Adverse Reactions (6)].

Do not apply to the diaper area; diapers or plastic pants may constitute occlusive use. [see Warnings and Precautions (5.1)]

3 DOSAGE FORMS AND STRENGTHS

DERMA-SMOOTHE/FS Scalp Oil is a topical oil containing 0.01% fluocinolone acetonide, supplied in bottles containing 4 fluid ounces and with 2 shower caps.

4 CONTRAINDICATIONS

None.

5 WARNINGS AND PRECAUTIONS

5.1 Endocrine System Adverse Reactions

Systemic absorption of topical corticosteroids can produce reversible hypothalamic-pituitary-adrenal (HPA) axis suppression with the potential for glucocorticosteroid insufficiency. Cushing's syndrome, hyperglycemia, and glucosuria can result from systemic absorption of topical corticosteroids.

HPA axis suppression and Cushing's syndrome have been reported in patients receiving topical corticosteroids.

Conditions which increase systemic absorption include the use of more potent corticosteroids, use over large surface areas, use over prolonged periods, use of occlusive dressings, altered skin barrier, liver failure, and young age. Use of more than one corticosteroid-containing product at the same time may increase total systemic corticosteroid exposure. Because of the potential for systemic absorption, use of topical corticosteroids may require that patients be periodically evaluated for HPA axis suppression. The ACTH stimulation test may be helpful in evaluating patients for HPA axis suppression.

If HPA axis suppression is documented, an attempt should be made to withdraw the drug, to reduce the frequency of application, or to substitute a less potent corticosteroid. Manifestations of adrenal insufficiency may require supplemental systemic corticosteroids. Recovery of HPA axis function is generally prompt upon discontinuation of topical corticosteroids.

5.2 Local Adverse Reactions

Local adverse reactions may occur with use of topical corticosteroids, including Derma-Smoothe/FS Scalp Oil, and may be more likely to occur with occlusive use, prolonged use or use of higher potency corticosteroids. Some local adverse reactions may be irreversible. Reactions may include atrophy, striae, telangiectasias, burning, itching, irritation, dryness, folliculitis, acneiform eruptions, hypopigmentation, perioral dermatitis, allergic contact dermatitis, secondary infection, and miliaria [see Adverse Reactions (6.1)].

5.3 Ophthalmic Adverse Reactions

Use of topical corticosteroids may increase the risks of glaucoma and posterior subcapsular cataract. Glaucoma and cataracts have been reported in postmarketing experience with the use of topical corticosteroid products. Avoid contact of DERMA-SMOOTHE/FS Scalp Oil with eyes. Advise patients to report any visual symptoms and consider referral to an ophthalmologist for evaluation.

5.4 Allergic Contact Dermatitis

Use of topical corticosteroids can cause allergic contact dermatitis. Allergic contact dermatitis to any component of topical corticosteroids is usually diagnosed by a failure to heal rather than a clinical exacerbation. Clinical diagnosis of allergic contact dermatitis can be confirmed by patch testing.

5.5 Concomitant Skin Infections

Use of topical corticosteroids may delay healing or worsen concomitant skin infections. Treat concomitant skin infections with an appropriate antimicrobial agent. If the infection persists unchanged, discontinue DERMA-SMOOTHE/FS Scalp Oil until the infection has been adequately treated.

5.6 Use in Peanut-Sensitive Individuals

Use caution in prescribing DERMA-SMOOTHE/FS Scalp Oil for peanut-sensitive individuals [see Description (11)].

Should signs of hypersensitivity present (wheal and flare reactions, pruritus, or other manifestations), or should disease exacerbations occur, discontinue DERMA-SMOOTHE/FS Scalp Oil immediately and institute appropriate therapy.

6 ADVERSE REACTIONS

The following serious adverse reactions are discussed in more detail in other sections of the labeling:
• Endocrine System Adverse Reactions [see Warnings and Precautions (5.1)]
• Local Adverse Reactions [see Warnings and Precautions (5.2)]
• Ophthalmic Adverse Reactions [see Warnings and Precautions (5.3)]

6.1 Clinical Studies Experience

Because clinical trials are conducted under widely varying condition, adverse reaction rates observed in the clinical trials of a drug cannot be directly compared to rates in the clinical trials of another drug and may not reflect the rates observed in practice.

An open-label safety study was conducted in 29 pediatric subjects 3 months to 2 years old to assess the HPA axis by ACTH stimulation testing following use of the formulation of DERMA-SMOOTHE/FS Scalp Oil twice daily for 4 weeks. DERMA-SMOOTHE/FS Scalp Oil is not approved for use in pediatric patients for the treatment of psoriasis of the scalp. The most common adverse reactions were reported in the study:

Table 1: Adverse Reactions in ≥2% Pediatric Subjects 3 Months to 2 Years of Age Treated with the Formulation of DERMA-SMOOTHE/FS Scalp Oil, N=30 [Includes one subject who withdrew at Week 2]
Adverse Reaction |  | n (%)
Cough |  | 6 (20)
Rhinorrhea |  | 4 (13)
Pyrexia |  | 3 (10)
Nasopharyngitis |  | 2 (7)
Hypopigmentation |  | 2 (7)
Abscess |  | 1 (3)
Atopic Dermatitis |  | 1 (3)
Eczema |  | 1 (3)
Hyperpigmentation |  | 1 (3)
Molluscum |  | 1 (3)
Rash |  | 1 (3)
Diarrhea |  | 1 (3)
Otitis Media |  | 1 (3)
URI |  | 1 (3)
Vomiting |  | 1 (3)

6.2 Postmarketing Experience

The following adverse reactions have been identified during post-approval use of products containing topical corticosteroids. Because postmarketing adverse reactions are reported voluntarily from a population of uncertain size, it is not always possible to reliably estimate their frequency or establish a causal relationship to drug exposure.

- Endocrine Disorders: HPA axis suppression and Cushing’s syndrome
- Eye Disorders: glaucoma and cataracts
- Nervous System Disorders: intracranial hypertension including bulging fontanelles, headaches, and bilateral papilledema

8 USE IN SPECIFIC POPULATIONS

8.1 Pregnancy

Risk Summary

Available data from case reports, case series, and observational studies on fluocinolone acetonide use in pregnant women have not identified a drug-associated risk of major birth defects, miscarriage or adverse maternal or fetal outcomes. Observational studies suggest maternal use of high to super-high potency topical steroids may be associated with an increased risk of low birthweight infants. Advise pregnant women to use DERMA-SMOOTHE/FS Scalp Oil on the smallest area of skin and for the shortest duration possible.

Corticosteroids can cause fetal malformations in laboratory animals when administered systemically at relatively low dosage levels. Some corticosteroids cause fetal malformations after dermal application in laboratory animals.

The background risk of major birth defects and miscarriage for the indicated population is unknown. All pregnancies have a background risk of birth defect, loss, or other adverse outcomes. In the U.S. general population, the estimated background risk of major birth defects and miscarriage in clinically recognized pregnancies is 2 to 4% and 15 to 20%, respectively.

8.2 Lactation

Risk Summary

There is no information regarding the presence of fluocinolone acetonide in breast milk or its effects on the breastfed infant or on milk production. It is not known whether topical administration of corticosteroids could result in sufficient systemic absorption to produce detectable quantities in breast milk. To minimize potential exposure to the breastfed infant via breast milk, use DERMA-SMOOTHE/FS Scalp Oil on the smallest area of skin and for the shortest duration possible while breastfeeding. Advise breastfeeding women not to apply DERMA-SMOOTHE/FS Scalp Oil directly to the nipple and areola to avoid direct infant exposure [see Warnings and Precautions (5.1)]. The developmental and health benefits of breastfeeding should be considered along with the mother's clinical need for DERMA-SMOOTHE/FS Scalp Oil and any potential adverse effects on the breastfed infant from DERMA-SMOOTHE/FS Scalp Oil or from the underlying maternal condition.

8.4 Pediatric Use

The safety and effectiveness of DERMA-SMOOTHE/FS Scalp Oil have not been established in pediatric patients with psoriasis of the scalp.

Evaluation in Peanut-Sensitive Pediatric Patients
A clinical trial was conducted to assess the safety of the formulation of DERMA-SMOOTHE/FS Scalp Oil, which contains refined peanut oil, in patients with known peanut allergies. The trial enrolled 13 pediatric subjects with atopic dermatitis, 6 to 17 years of age. DERMA-SMOOTHE/FS Scalp Oil is not approved for the treatment of atopic dermatitis. Of the 13 subjects, 9 were Radioallergosorbent Test (RAST) positive to peanuts and 4 had no peanut sensitivity (controls). The trial evaluated the subjects’ responses to both prick test and patch test utilizing refined peanut oil, the formulation of DERMA-SMOOTHE/FS Scalp Oil and histamine/saline controls. Subjects were also treated with the formulation of DERMA-SMOOTHE/FS Scalp Oil twice daily for 7 days. Prick test and patch test results for all 13 subjects were negative to the formulation of DERMA-SMOOTHE/FS Scalp Oil and the refined peanut oil. One of the 9 peanut-sensitive subjects experienced an exacerbation of atopic dermatitis after 5 days of use on the formulation of DERMA-SMOOTHE/FS Scalp Oil.

11 DESCRIPTION

DERMA-SMOOTHE/FS Scalp Oil (fluocinolone acetonide) topical oil, 0.01% contains fluocinolone acetonide [(6α, 11β, 16α)-6,9-difluoro-11,21-dihydroxy-16,17[(1–methylethylidene) bis(oxy)]-pregna-1,4-diene-3,20-dione, cyclic 16,17 acetal with acetone], a synthetic corticosteroid for topical dermatologic use. Chemically, fluocinolone acetonide is C24 H30 F2 O6. It has the following structural formula:

Fluocinolone acetonide has a molecular weight of 452.50. It is a white crystalline powder that is odorless, stable in light, and melts at 270°C with decomposition; soluble in alcohol, acetone and methanol; slightly soluble in chloroform; insoluble in water.

Each gram of DERMA-SMOOTHE/FS Scalp Oil contains approximately 0.11 mg of fluocinolone acetonide in a blend of oils, which contains isopropyl alcohol, isopropyl myristate, light mineral oil, oleth-2, refined peanut oil and fragrances.

Each packaged product contains 2 shower caps. The shower cap is made of low density polyethylene material with rubber elastic.

DERMA-SMOOTHE/FS Scalp Oil is formulated with 48% refined peanut oil. The bulk refined peanut oil used in DERMA-SMOOTHE/FS Scalp Oil is heated at 246°C (475°F) for at least 15 minutes. The refined peanut oil used in DERMA-SMOOTHE/FS Scalp Oil is routinely tested for peanut proteins through amino acid analysis; the quantity of amino acids is below 0.5 parts per million (ppm).

12 CLINICAL PHARMACOLOGY

12.1 Mechanism of Action

Corticosteroids play a role in cellular signaling, immune function, inflammation, and protein regulation; however, the precise mechanism of action in psoriasis of the scalp is unknown.

12.2 Pharmacodynamics

Vasoconstrictor Assay
DERMA-SMOOTHE/FS Scalp Oil is in the low to medium range of potency as compared with other topical corticosteroids in vasoconstrictor studies. However, similar blanching scores do not necessarily imply therapeutic equivalence.

Hypothalamic-Pituitary-Adrenal (HPA) Axis Suppression
HPA axis suppression following administration of DERMA-SMOOTHE/FS Scalp Oil was not assessed.

12.3 Pharmacokinetics

Topical corticosteroids can be absorbed from intact healthy skin. The extent of percutaneous absorption of topical corticosteroids is determined by many factors, including the product formulation and the integrity of the epidermal barrier. Occlusion, inflammation and/or other disease processes in the skin may increase percutaneous absorption. The use of pharmacodynamic endpoints for assessing the systemic exposure of topical corticosteroids may be necessary due to the fact that circulating levels are often below the level of detection. Once absorbed through the skin, topical corticosteroids are metabolized, primarily in the liver, and are then excreted by the kidneys. Some corticosteroids and their metabolites are also excreted in the bile.

13 NONCLINICAL TOXICOLOGY

13.1 Carcinogenesis, mutagenesis, impairment of fertility

No carcinogenicity, genotoxicity, or fertility studies were conducted with DERMA-SMOOTHE/FS Scalp Oil. However, some corticosteroids are genotoxic in various genotoxicity tests (i.e., the in vitro human peripheral blood lymphocyte chromosome aberration assay with metabolic activation, the in vivo mouse bone marrow micronucleus assay, the Chinese hamster micronucleus test, and the in vitro mouse lymphoma gene mutation assay).

14 CLINICAL STUDIES

In a vehicle-controlled study for the treatment of psoriasis of the scalp in adults, after 21 days of treatment, 60% of patients on active treatment and 21% of patients on the drug vehicle had excellent to cleared clinical response.

16 HOW SUPPLIED / STORAGE AND HANDLING

DERMA-SMOOTHE/FS Scalp Oil (fluocinolone acetonide) topical oil, 0.01% (NDC # 68791-102-04) is supplied in bottles containing 4 fluid ounces and with 2 shower caps.

STORAGE AND HANDLING

Storage: Keep tightly closed. Store at 20°-25°C (68°-77°F); excursions permitted to 15°-30°C (59°-86°F) [see USP Controlled Room Temperature].

17 PATIENT COUNSELING INFORMATION

Administration Instructions
Advise patients that DERMA-SMOOTHE/FS Scalp Oil is for topical use only [see Dosage and Administration (2)].

Instruct patients not to apply DERMA-SMOOTHE/FS Scalp Oil to the diaper area as diapers or plastic pants may constitute occlusive use [see Dosage and Administration (2)].

Advise patients to avoid use of DERMA-SMOOTHE/FS Scalp Oil on the face, axillae, or groin unless directed by their healthcare provider [see Dosage and Administration (2)].

Advise patients to discontinue therapy when control of disease is achieved. Instruct patients to contact their healthcare provider if no improvement is seen within 2 weeks [see Dosage and Administration (2)].

Endocrine System Adverse Reactions
Instruct patients not to use other corticosteroid-containing products while using DERMA-SMOOTHE/FS Scalp Oil without first consulting their healthcare provider [see Warnings and Precautions (5.1)].

Ophthalmic Adverse Reactions
Advise patients to avoid contact with the eyes and in case of contact, wash eyes liberally with water. Instruct patients to tell their healthcare provider if they develop any visual symptoms [see Warnings and Precautions (5.3)].

Pregnancy and Lactation
Advise women to use DERMA-SMOOTHE/FS Scalp Oil on the smallest area of skin and for the shortest duration possible while pregnant or breastfeeding. Advise patients that are breastfeeding not to apply DERMA-SMOOTHE/FS Scalp Oil directly to the nipple and areola to avoid direct infant exposure [See Use in Specific Populations (8.1 and 8.2)].

Manufactured by:
Hill Dermaceuticals, Inc.
Sanford, Florida 32773

For:
Royal Pharmaceutical, Inc.
Wall, NJ 07719

Rev. CODE 171A239-2

Date: 08/2024

DERMA-SMOOTHE/FS is a registered trademark of Hill Dermaceuticals, Inc.
© 2024 Hill Dermaceuticals, Inc. All rights reserved.

PRINCIPAL DISPLAY PANEL - 118.28 mL Carton Label

NDC 68791-102-04

Rx only

Derma-Smoothe/FS®

Fluocinolone Acetonide
0.01% Topical Oil

(SCALP OIL)

FOR TOPICAL USE ONLY

NOT FOR ORAL, OPHTHALMIC,
OR INTRAVAGINAL USE

SHAKE WELL BEFORE USE

Net Contents 118.28 mL
(4 Fl. oz.)

ROYAL
PHARMACEUTICALS®

PRINCIPAL DISPLAY PANEL - 20 mL Carton Physcian Sample Label

NOT FOR SALE

PHYSICIAN SAMPLE

NDC 68791-102-01

Rx only

Derma-Smoothe/FS®

Fluocinolone Acetonide 0.01% Topical Oil

(SCALP OIL)

FOR TOPICAL USE ONLY

NOT FOR ORAL OPHTHALMIC,

OR INTRAVAGINAL USE

SHAKE WELL BEFORE USE

NET Contents: 20 mL

Royal Pharmaceuticals®